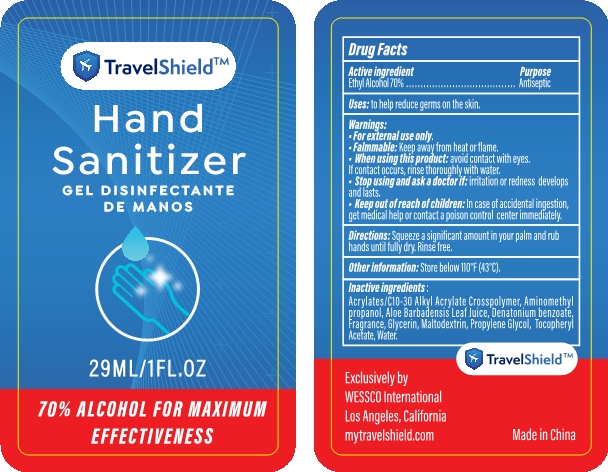 DRUG LABEL: Hand Sanitizer
NDC: 74934-090 | Form: GEL
Manufacturer: Zhejiang iColor Biotech Co., Ltd
Category: otc | Type: HUMAN OTC DRUG LABEL
Date: 20210803

ACTIVE INGREDIENTS: ALCOHOL 70 mL/100 mL
INACTIVE INGREDIENTS: CARBOMER INTERPOLYMER TYPE A (55000 CPS); GLYCERIN; PROPYLENE GLYCOL; WATER; DENATONIUM BENZOATE; AMINOMETHYLPROPANOL; FRAGRANCE LAVENDER & CHIA F-153480; ALOE VERA LEAF; .ALPHA.-TOCOPHEROL ACETATE; MALTODEXTRIN

Zhejiang iColor Biotech Co., Ltd
Hand Sanitizer 29ml

Active Ingredient(s)

Ethyl Alcohol 70% v/v.

Purpose

Antiseptic

Use

to help reduce germs on the skin.

Warnings

- For external use only.
- Flammable: Keep away from heat or flame.

When using this product: avoid contact with eyes. lf contact occurs, rinse thoroughly with water.

STOP USE

Stop using and ask a doctor if irritation or redness develops and lasts.

Keep out of reach of children: ln case of accidental ingestion, get medical help or contact a poison control center immediately.

Directions

- Squeeze a significant amount in your palm and rub hands until fully dry.
- Rinse free.

Other information

- Store below 110 °F（43° C).

Inactive ingredients

Acrylates/C10-30 Alkyl Acrylate Crosspolymer, Aminomethyl propanol, Aloe Barbadensis leaf Juice, Denatonium benzoate, Fragrance, Glycerin, Maltodextrin, Propylene Glycol, Tocopheryl Acetate, Water.

Package Label - Principal Display Panel

29 mL NDC: 74934-090-01